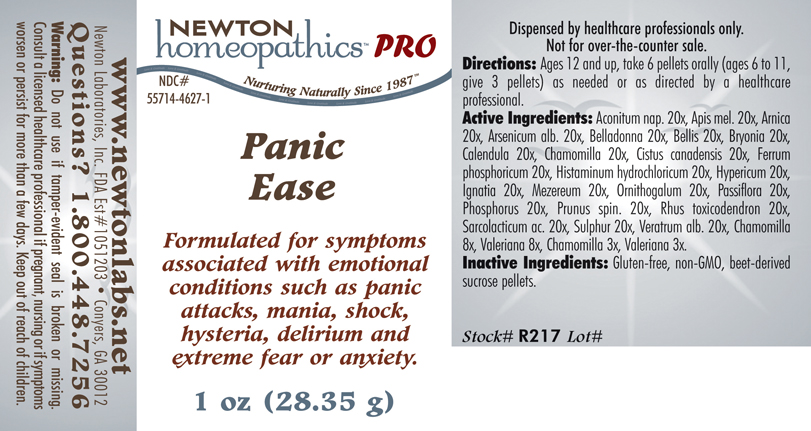 DRUG LABEL: Panic Ease 
NDC: 55714-4627 | Form: PELLET
Manufacturer: Newton Laboratories, Inc.
Category: homeopathic | Type: HUMAN PRESCRIPTION DRUG LABEL
Date: 20110601

ACTIVE INGREDIENTS: Aconitum Napellus 20 [hp_X]/1 g; Apis Mellifera 20 [hp_X]/1 g; Arnica Montana 20 [hp_X]/1 g; Arsenic Trioxide 20 [hp_X]/1 g; Atropa Belladonna 20 [hp_X]/1 g; Bellis Perennis 20 [hp_X]/1 g; Bryonia Alba Root 20 [hp_X]/1 g; Calendula Officinalis Flowering Top 20 [hp_X]/1 g; Matricaria Recutita 20 [hp_X]/1 g; Helianthemum Canadense 20 [hp_X]/1 g; Ferrosoferric Phosphate 20 [hp_X]/1 g; Histamine Dihydrochloride 20 [hp_X]/1 g; Hypericum Perforatum 20 [hp_X]/1 g; Strychnos Ignatii Seed 20 [hp_X]/1 g; Daphne Mezereum Bark 20 [hp_X]/1 g; Ornithogalum Umbellatum 20 [hp_X]/1 g; Passiflora Incarnata Flowering Top 20 [hp_X]/1 g; Phosphorus 20 [hp_X]/1 g; Prunus Spinosa Flower Bud 20 [hp_X]/1 g; Toxicodendron Pubescens Leaf 20 [hp_X]/1 g; Lactic Acid, L- 20 [hp_X]/1 g; Sulfur 20 [hp_X]/1 g; Veratrum Album Root 20 [hp_X]/1 g; Valerian 8 [hp_X]/1 g
INACTIVE INGREDIENTS: Sucrose

Panic Ease

INDICATIONS & USAGE SECTION

Panic Ease Formulated for symptoms associated with emotional conditions such as panic attacks, mania, shock, hysteria, delirium and extreme fear or anxiety.

DOSAGE & ADMINISTRATION SECTION

Directions: Ages 12 and up, take 6 pellets orally (ages 6 to 11, give 3 pellets) as needed or as directed by a healthcare professional.

ACTIVE INGREDIENT SECTION

Aconitum nap. 20x, Apis mel. 20x, Arnica 20x, Arsenicum alb. 20x, Belladonna 20x, Bellis 20x, Bryonia 20x, Calendula 20x, Chamomilla 20x, Cistus canadensis 20x, Ferrum phosphoricum 20x, Histaminum hydrochloricum 20x, Hypericum 20x, Ignatia 20x, Mezereum 20x, Ornithogalum 20x, Passiflora 20x, Phosphorus 20x, Prunus spin. 20x, Rhus toxicodendron 20x, Sarcolacticum ac. 20x, Sulphur 20x, Veratrum alb. 20x, Chamomilla 8x, Valeriana 8x, Chamomilla 3x, Valeriana 3x.

PURPOSE SECTION

Formulated for symptoms associated with emotional conditions such as panic attacks, mania, shock, hysteria, delirium and extreme fear or anxiety.

INACTIVE INGREDIENT SECTION

Inactive Ingredients: Gluten-free, non-GMO, beet-derived sucrose pellets.

QUESTIONS? SECTION

www.newtonlabs.net Newton Laboratories, Inc. FDA Est # 1051203 - Conyers, GA 30012
Questions? 1.800.448.7256

WARNINGS SECTION

Warning: Do not use if tamper - evident seal is broken or missing. Consult a licensed healthcare professional if pregnant, nursing or if symptoms worsen or persist for more than a few days. Keep out of reach of children.

PREGNANCY OR BREAST FEEDING SECTION

Consult a licensed healthcare professional if pregnant, nursing or if symptoms worsen or persist for more than a few days.

KEEP OUT OF REACH OF CHILDREN SECTION

Keep out of reach of children